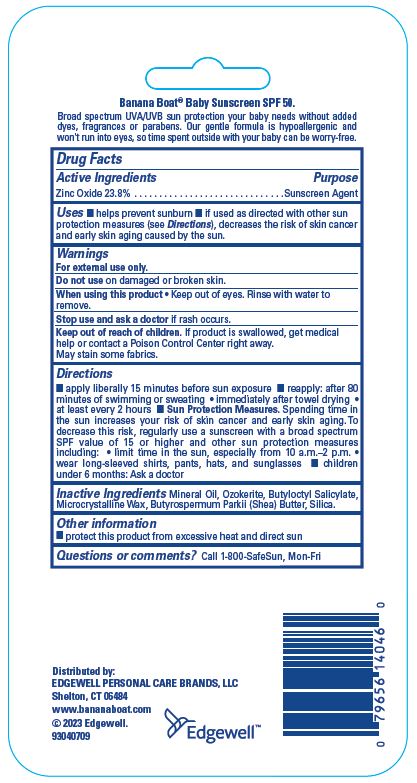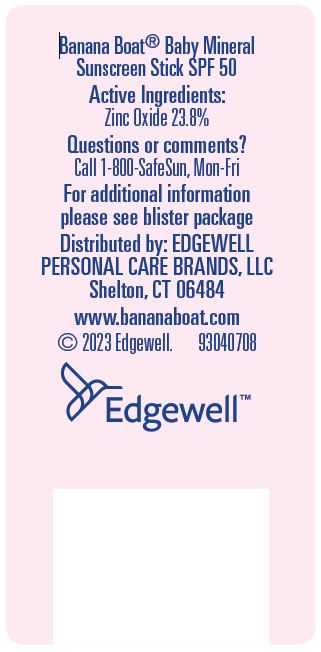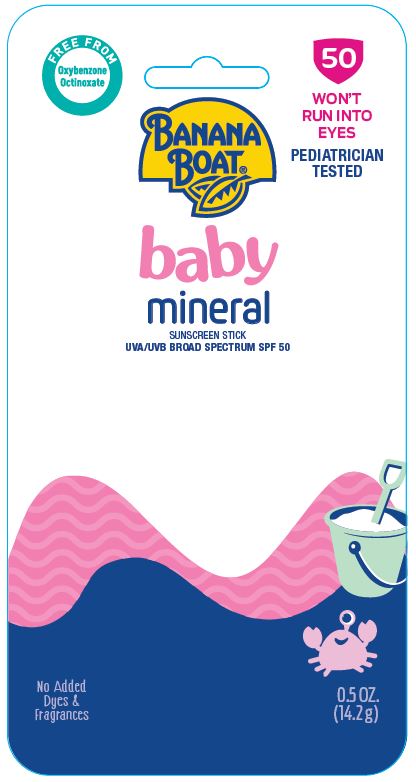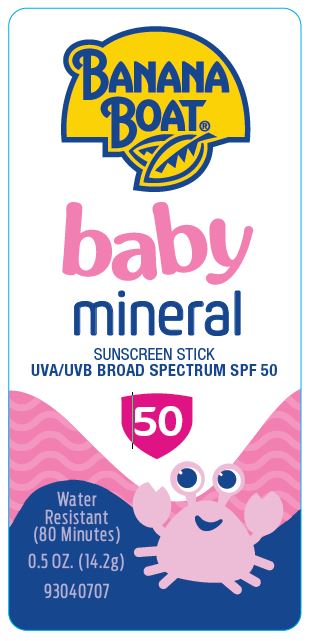 DRUG LABEL: BANANA BOAT
NDC: 63354-164 | Form: STICK
Manufacturer: Edgewell Personal Care Brands LLC
Category: otc | Type: HUMAN OTC DRUG LABEL
Date: 20231003

ACTIVE INGREDIENTS: ZINC OXIDE 23.8 g/100 g
INACTIVE INGREDIENTS: SHEA BUTTER; SILICON DIOXIDE; CERESIN; BUTYLOCTYL SALICYLATE; MICROCRYSTALLINE WAX; MINERAL OIL

Active Ingredients

Zinc Oxide 23.8%

Purpose

Sunscreen Agent

Uses

• helps prevent sunburn • if used as directed with other sun protection measures (see Directions), decreases the risk of skin cancer and early skin aging caused by the sun

Warnings

For external use only

May stain some fabrics.

Do not use

on damaged or broken skin.

When using this product

• Keep out of eyes. Rinse with water to remove.

Stop use and ask a doctor

if rash occurs.

Keep out of reach of children.

If product is swallowed, get medical help or contact a Poison Control Center right away.

Directions

• apply liberally 15 minutes before sun exposure • reapply: after 80 minutes of swimming or sweating • immediately after towel drying • at least every 2 hours • Sun Protection Measures. Spending time in the sun increases your risk of skin cancer and early skin aging. To decrease this risk, regularly use a sunscreen with a broad spectrum SPF value of 15 or higher and other sun protection measures including: • limit time in the sun, especially from 10 a.m.–2 p.m. • wear long-sleeved shirts, pants, hats, and sunglasses • children under 6 months: Ask a doctor

Inactive Ingredients

Mineral Oil, Ozokerite, Butyloctyl Salicylate, Microcrystalline Wax, Butyrospermum Parkii (Shea) Butter, Silica.

Other information

• protect this product from excessive heat and direct sun

Questions or comments?

Call 1-800-SafeSun, Mon-Fri

Principal Display Panel

BANANA BOAT(R)
baby
mineral
SUNSCREEN STICK
UVA/UVB BROAD SPECTRUM SPF 50
50
Water
Resistant
(80 Minutes)
0.5 OZ. (14.2g)
93040707

FREE FROM
Oxybenzone
Octinoxate
50
BANANA BOAT(R)
WONT
RUN INTO
EYES
PEDIATRICIAN
TESTED
baby
mineral
SUNSCREEN STICK
UVA/UVB BROAD SPECTRUM SPF 50
No Added
Dyes &
Fragrances
0.5 OZ.
(14.2.g)